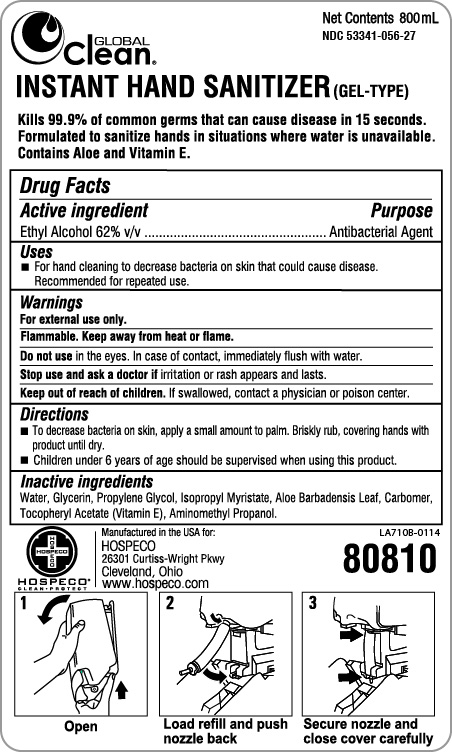 DRUG LABEL: Instant Hand Sanitizer (Gel-Type)
NDC: 53341-056 | Form: SOLUTION
Manufacturer: Tranzonic Companies
Category: otc | Type: HUMAN OTC DRUG LABEL
Date: 20140227

ACTIVE INGREDIENTS: ALCOHOL 62 mL/100 mL
INACTIVE INGREDIENTS: WATER; POLYACRYLIC ACID (250000 MW); GLYCERIN; PROPYLENE GLYCOL; ISOPROPYL MYRISTATE; AMINOMETHYLPROPANOL; ALOE VERA LEAF; ALPHA-TOCOPHEROL ACETATE

Instant Hand Sanitizer (Gel-Type)

ACTIVE INGREDIENT

Ethyl Alcohol 62% v/v.....Antibacterial Agent

INACTIVE INGREDIENT

Water, Glycerin, Propylene Glycol, Isopropyl Myristate, Aloe Barbadensis Leaf, Carbomer, Tocopheryl Acetate (Vitamin E), Aminomethyl Propanol

PURPOSE

For hand cleaning to decrease bacteria on skin that could cause disease. Recommended for repeated use.

WARNINGS

For external use only.

Flammable. Keep away from heat or flame.

Do not use in the eyes. In case of contact, immediately flush with water.

Stop use and ask a doctor if irritation or rash appears and lasts.

Keep out of reach of children. If swallowed, contact a physician or poison center.

DOSAGE AND ADMINISTRATION

To decrease bacteria on skin, apply a small amount to palm. Briskly rub, covering hands with product until dry.

Children under 6 years of age should be supervised when using this product.

INDICATIONS AND USAGE

For hand cleaning to decrease bacteria on skin that could cause disease.

Do not use in the eyes. In case of contact, immediately flush with water.

Stop use and ask a doctor if irritation or rash appears and lasts.

Keep out of reach of children. If swallowed, contact a physician or poison center.

Keep out of reach of children. If swallowed, contact a physician or poison center.

PACKAGE LABEL

53341-056-27.jpg